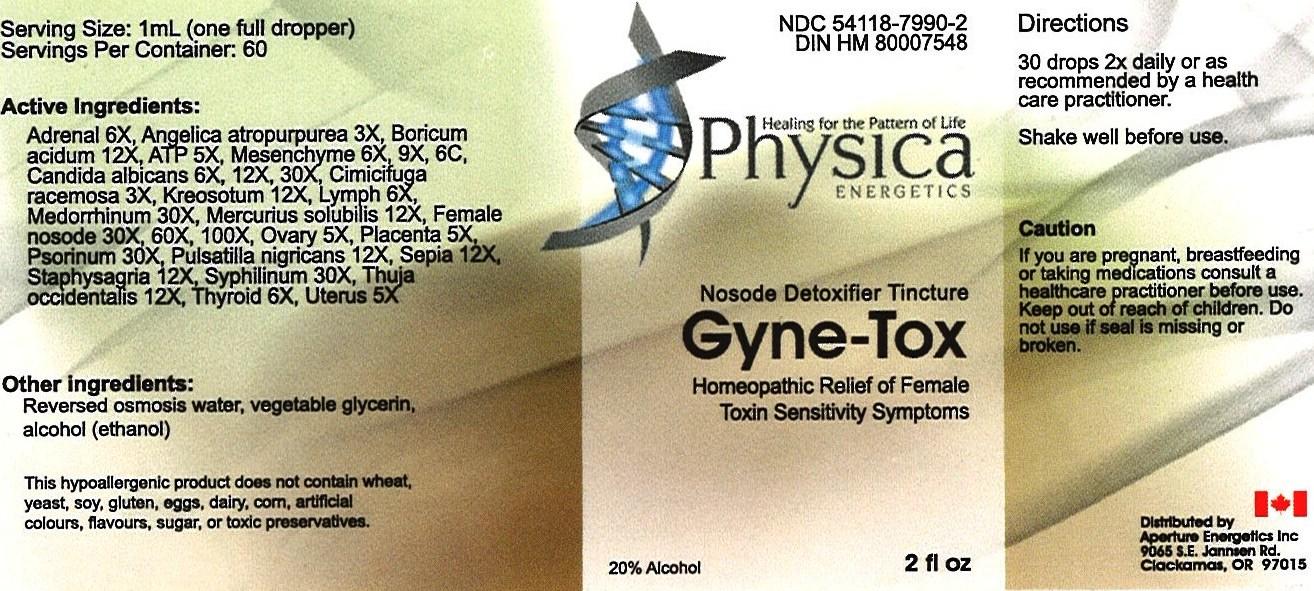 DRUG LABEL: Gyne - Tox
                
NDC: 54118-7990 | Form: SOLUTION/ DROPS
Manufacturer: ABCO Laboratories, Inc.
Category: homeopathic | Type: HUMAN OTC DRUG LABEL
Date: 20121219

ACTIVE INGREDIENTS: BOS TAURUS ADRENAL GLAND 6 [hp_X]/60 mL; ANGELICA ATROPURPUREA ROOT 3 [hp_X]/60 mL; BORIC ACID 12 [hp_X]/60 mL; ADENOSINE TRIPHOSPHATE 5 [hp_X]/60 mL; BOS TAURUS MESENCHYME 6 [hp_X]/60 mL; CANDIDA ALBICANS 6 [hp_X]/60 mL; BLACK COHOSH 3 [hp_X]/60 mL; WOOD CREOSOTE 12 [hp_X]/60 mL; BOS TAURUS LYMPH 6 [hp_X]/60 mL; GONORRHEAL URETHRAL SECRETION HUMAN 30 [hp_X]/60 mL; MERCURIUS SOLUBILIS 12 [hp_X]/60 mL; ESTRONE 30 [hp_X]/60 mL; BOS TAURUS OVARY 5 [hp_X]/60 mL; BOS TAURUS PLACENTA 5 [hp_X]/60 mL; SCABIES LESION LYSATE (HUMAN) 30 [hp_X]/60 mL; ANEMONE NEMOROSA 12 [hp_X]/60 mL; SEPIA OFFICINALIS JUICE 12 [hp_X]/60 mL; DELPHINIUM STAPHISAGRIA SEED 12 [hp_X]/60 mL; TREPONEMIC SKIN CANKER HUMAN 30 [hp_X]/60 mL; THUJA OCCIDENTALIS LEAFY TWIG 12 [hp_X]/60 mL; THYROID, UNSPECIFIED 6 [hp_X]/60 mL; BOS TAURUS UTERUS 5 [hp_X]/60 mL
INACTIVE INGREDIENTS: WATER; GLYCERIN; ALCOHOL

Gyne Tox

Active Ingredients:

- Adrenal 6x
- Angelica atropurpurea 3x
- Boricum acidum 12x
- ATP 5x
- Mesenchyme 6x, 9x, 6c
- Candida albicans 6x, 12x, 30x
- Cimicifuga racemosa 3x
- Kreosotum 12x
- Lymph 6x
- Medorrhinum 30x
- Mercurius solubilis 12x
- Female nosode 30x, 6x, 100x
- Ovary 5x
- Placenta 5x
- Psorinum 30x
- Pulsatilla nigricans 12x
- Sepia 12x
- Staphysagria 12x
- Syphilinum 30x
- Thuja occidentalis 12x
- Thyroid 6x
- Uterus 5x

PURPOSE

- Homeopathic Relief of Female Toxin Sensitivity Symptoms

- Keep out of reach of children

INDICATIONS AND USAGE

- 30 drops 2X daily
- or as recommended by a health care practitioner
- Shake well before use

WARNINGS

- If you are pregnant, breastfeeding or taking medications consult a health care practitioner before use.
- Keep out of reach of children
- Do not use if seal is missing or broken

DOSAGE AND ADMINISTRATION

- 30 drops 2X daily
- or as recommended by a health care practitioner
- Shake well before use

INACTIVE INGREDIENT

- Reverse osmosis water
- Vegetabe glycerin
- Alcohol (ethanol)

PACKAGE LABEL

- bottle image/jpeg
- gynelabel.jpg